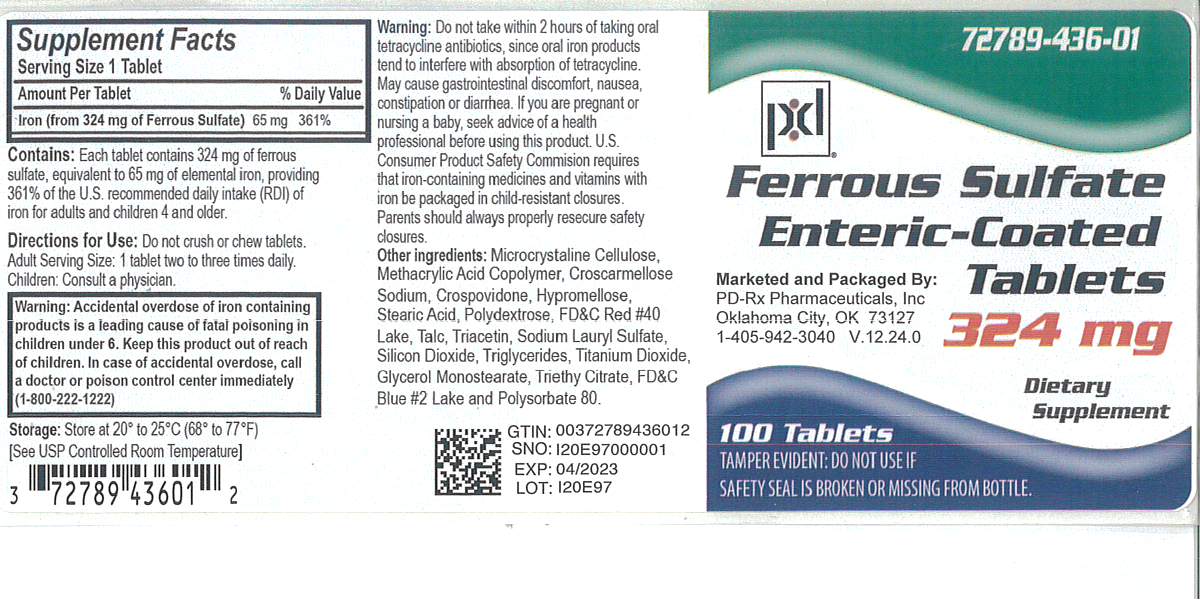 DRUG LABEL: Ferrous Sulfate
NDC: 72789-436 | Form: TABLET
Manufacturer: PD-Rx Pharmaceuticals, Inc.
Category: other | Type: DIETARY SUPPLEMENT
Date: 20251203

ACTIVE INGREDIENTS: FERROUS SULFATE 65 mg/1 1
INACTIVE INGREDIENTS: MICROCRYSTALLINE CELLULOSE; METHACRYLIC ACID; CROSCARMELLOSE SODIUM; CROSPOVIDONE; HYPROMELLOSES; STEARIC ACID; POLYDEXTROSE; FD&C RED NO. 40 ALUMINUM LAKE; TALC; TRIACETIN; SODIUM LAURYL SULFATE; SILICON DIOXIDE; MEDIUM-CHAIN TRIGLYCERIDES; TITANIUM DIOXIDE; 1,2-DILINOLEOYL-3-OLEOYL-SN-GLYCEROL; TRIETHYL CITRATE; FD&C BLUE NO. 2--ALUMINUM LAKE; POLYSORBATE 80

FERROUS SULFATE
ENTERIC-COATED TABLETS

STATEMENT OF IDENTITY

Dietary Supplement

CONTAINS:

Each tablet contains 324 mg of ferrous sulfate, equivalent to 65 mg of elemental iron, providing 361% of the U.S. recommended daily intake (RDI) of iron for adults and children 4 and older.

DIRECTIONS FOR USE:

Do not crush or chew tablets. Adult Serving Size: 1 tablet two to three times daily. Children: Consult a physician.

WARNING:

Accidental overdose of iron containing products is a leading cause of fatal poisoning in children under 6. Keep this product out of reach of children. In case of accidental overdose, call a doctor or poison control center immediately (1-800-222-1222).

WARNINGS:

Do not take within 2 hours of taking oral tetracycline antibiotics, since oral iron products tend to interfere with absorption of tetracycline. May cause gastrointestinal discomfort, nausea, constipation or diarrhea. If you are pregnant or nursing a baby, seek advice of a health professional before using this product. U.S. Consumer Product Safety Commission requires that iron-containing medicines and vitamins with iron be packaged in child-resistant closures. Parents should always properly resecure safety closures.

STORAGE:

Store at 20° to 25°C (68° to 77°F) [see USP Controlled Room Temperature]

Supplement Facts

Serving Size 1 Tablet
Amount Per Tablet | % Daily Value
Iron (from 324 mg of Ferrous Sulfate) | 65 mg | 361%

Other ingredients:Microcrystalline Cellulose, Methacrylic Acid Copolymer, Croscarmellose Sodium. Crospovidone, Hypromellose, Stearic Acid, Polydextrose, FD&C Red #40 Lake, Talc, Triacetin, Sodium Lauryl Sulfate, Silicon Dioxide, Triglycerides, Titanium Dioxide, Glycerol Monostearate, Triethyl Citrate, FDC Blue #2 Lake and Polysorbate 80.

16 HOW SUPPLIED

Ferrous Sulfate Tablets are available as follows:

Each tablet contains 324mg of ferrous sulfate, equivalent to 65mg of elemental iron, providing 361% of the U.S. recommended daily intake (RDI) of iron for adults and children 4 and older.

Available in bottles of 100 tablets (72789-436-01)

PRINCIPAL DISPLAY PANEL - 324 mg Tablet Bottle Label

72789-436-01

Ferrous Sulfate
Enteric-Coated
Tablets

324 mg

Dietary
Supplement

Marketed and Packaged By:
PD-Rx Pharmaceuticals, Inc
Oklahoma City, OK 73127
1-405-942-3040 V.12.24.0

100 Tablets
TAMPER EVIDENT: DO NOT USE IF
SAFETY SEAL IS BROKEN OR MISSING FROM BOTTLE.